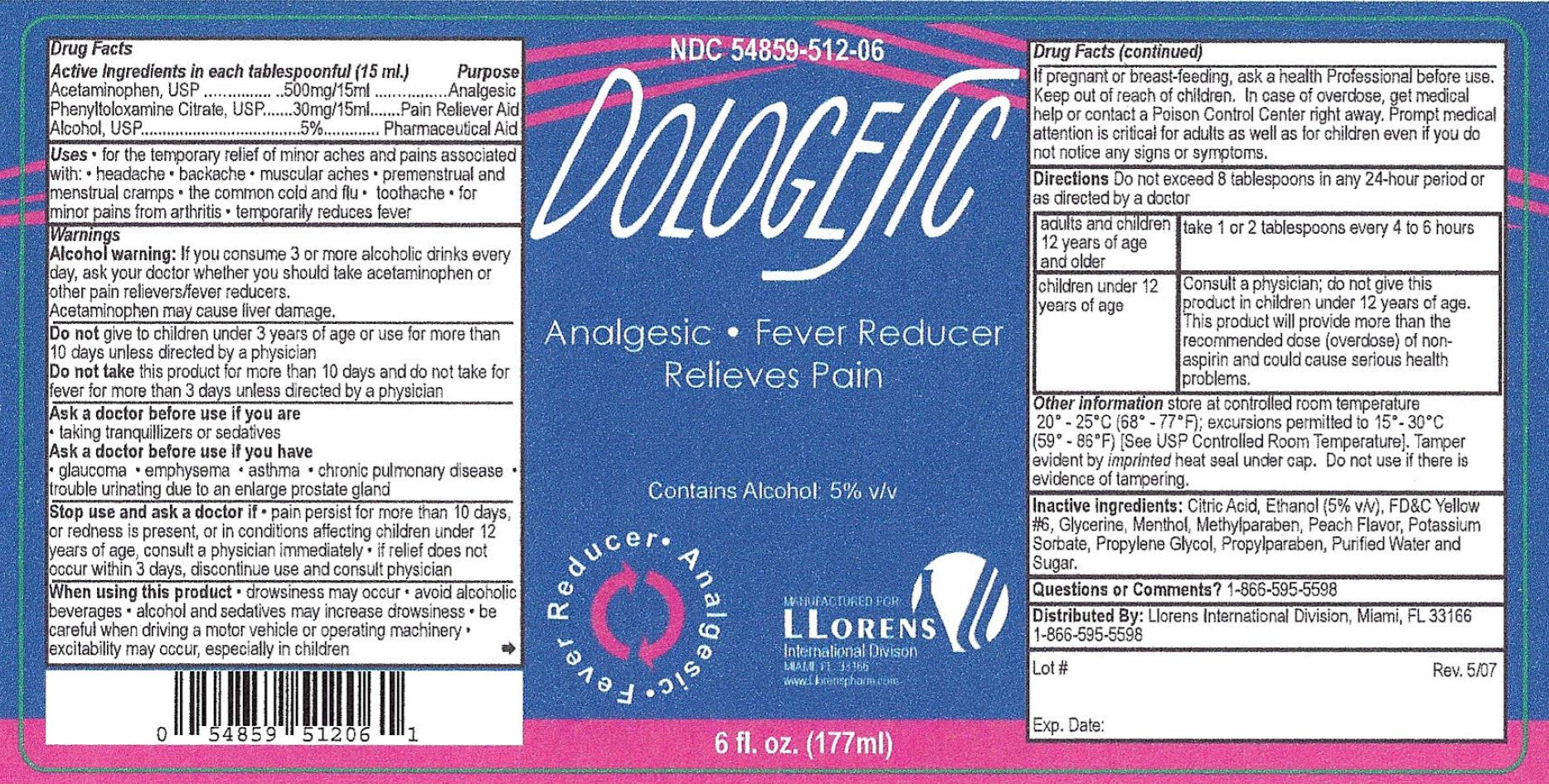 DRUG LABEL: Dologesic
NDC: 54859-512 | Form: LIQUID
Manufacturer:  Llorens Pharmaceutical International Division
Category: otc | Type: HUMAN OTC DRUG LABEL
Date: 20120619

ACTIVE INGREDIENTS: ACETAMINOPHEN 500 mg/15 mL; PHENYLTOLOXAMINE CITRATE 30 mg/15 mL; ALCOHOL 0.75 mL/15 mL
INACTIVE INGREDIENTS: CITRIC ACID MONOHYDRATE; ALCOHOL; GLYCERIN; FD&C YELLOW NO. 6; MENTHOL; METHYLPARABEN; POTASSIUM SORBATE; PROPYLENE GLYCOL; WATER; SUCROSE

Drug Facts

Active Ingredients in each tablespoonful (15 mL) Purpose

Acetaminophen, USP .................... 500 mg/15mL......................Pain Reliever/Fever Reducer

Phenyltoloxamine Citrate, USP ........ 30 mg/15mL......................Pain Reliever

Alcohol, USP....................................... 5%...............................Pharmaceutical Aid

Uses

- for the temporary relief of minor aches and pains associated with
-
  - headache
  - backache
  - muscular aches
  - premenstrual and menstrual cramps
  - the common cold and flu
  - toothache
  - for minor pains from arthritis
  - temporarily reduces fever

WARNINGS

Alcohol Warning:If you consumer 3 or more alcoholic drinks every day, ask your doctor whether you should take acetaminophen or other pain relievers/fever reducers.

Acetaminophen may cause liver damage.

When using this product

- drowsiness may occur
- avoid alcoholic beverages
- alcohol and sedatives may increase drowsiness
- be careful when driving a motor vehicle or operating machinery
- excitability may occur, especially in children

Ask a doctor before use if you are

- taking tranquilizers or sedatives

Ask a doctor before use if you have

- glaucoma
- emphysema
- asthma
- chronic pulmonary disease
- trouble urinating due to an enlarged prostate gland

Stop use and ask a doctor if

- pain persists for more than 10 days, or redness is present, or in conditions affecting children 12 years of age, consult a physician immediately
- if relief does not occur within 3 days, discontinue use and consult a physician

DO NOT USE

Do not give to children under 3 years of age or more use for more than 10 days unless directed by a physician

Do not take this product for more than 10 days and do not take for fever for more than 3 days unless directed by a physician

Keep out of reach of children. In case of overdose, get medical help or contact a Poison Control Center right away. Prompt medical attention is critical for adults as well as for children even if you do not notice any signs or symptoms.

PREGNANCY OR BREAST FEEDING

If pregnant or breast-feeding, ask a health professional before use.

DOSAGE AND ADMINISTRATION

Directions Do not exceed 8 tablespoons in any 24-hour period or as directed by a doctor

adults and children 12 years of age and older | take 1 or 2 tablespoons every 4 to 6 hours
children under 12 years of age | Consult a physician; do not give this product to children under 12 years of age. This product will provide more than the recommended dose (overdose) of non-aspirin and could cause serious health problems

Other information store at controlled room temperature 20 - 25 degrees C (68 - 77 degrees F); excursions permitted to 15 - 30 degrees C (59 - 86 degrees F) [See USP Controlled Room Temperature]. Tamper evident by imprinted heat seal under cap. Do not use if there is evidence of tampering.

INACTIVE INGREDIENT

Inactive ingredients:Citric Acid, Ethanol (5 percent by volume), FD and C Yellow Number 6, Glycerin, Menthol, Methylparaben, Peach Flavor, Potassium Sorbate, Propylene Glycol, Propylparaben, Purified Water and Sugar.

Questions or Comments? 1-866-595-5598

Llorens International Division, Miami, Fl 33166